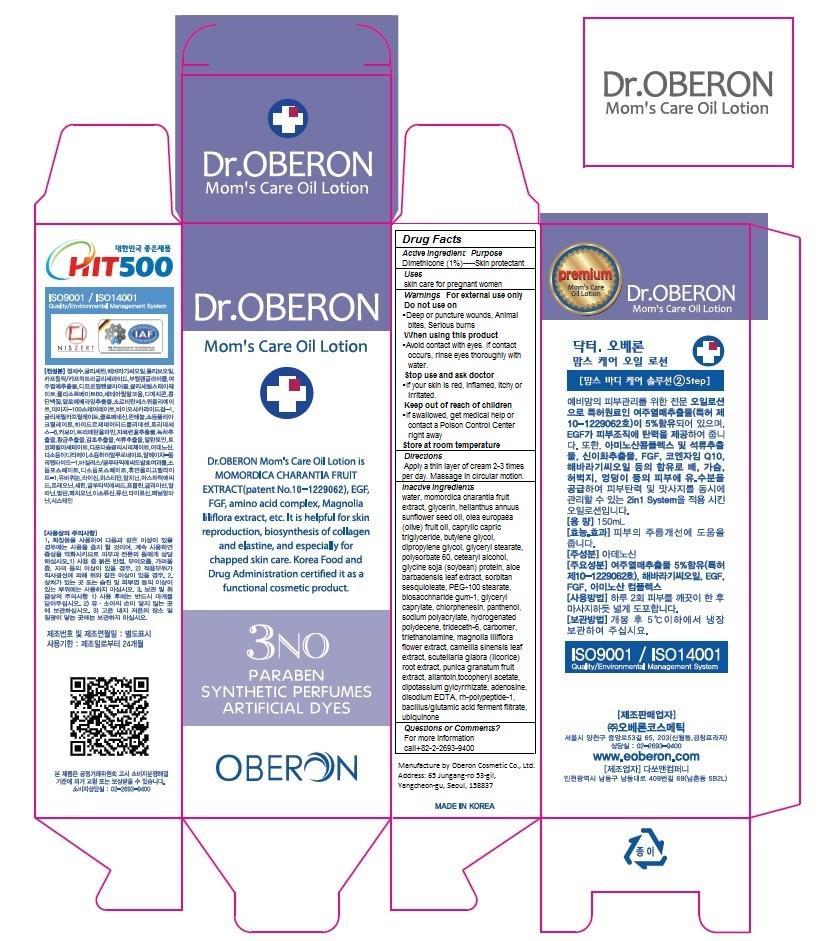 DRUG LABEL: Dr. OBERON MOMS CARE OIL
NDC: 52891-101 | Form: OIL
Manufacturer: Oberon Cosmetic Co., Ltd.
Category: otc | Type: HUMAN OTC DRUG LABEL
Date: 20140611

ACTIVE INGREDIENTS: dimethicone 1.5 1/150 mL
INACTIVE INGREDIENTS: water; MOMORDICA CHARANTIA FRUIT; GLYCERIN; HELIANTHUS ANNUUS SEED WAX; OLEA EUROPAEA FRUIT VOLATILE OIL; CAPRYLIC/CAPRIC/LAURIC TRIGLYCERIDE; butylene glycol; dipropylene glycol; GLYCERYL STEARATE CITRATE; polysorbate 60; SOYBEAN; ALOE; SORBITAN SESQUIOLEATE; PEG-100 stearate

Dr. OBERON MOM'S CARE OIL LOTION